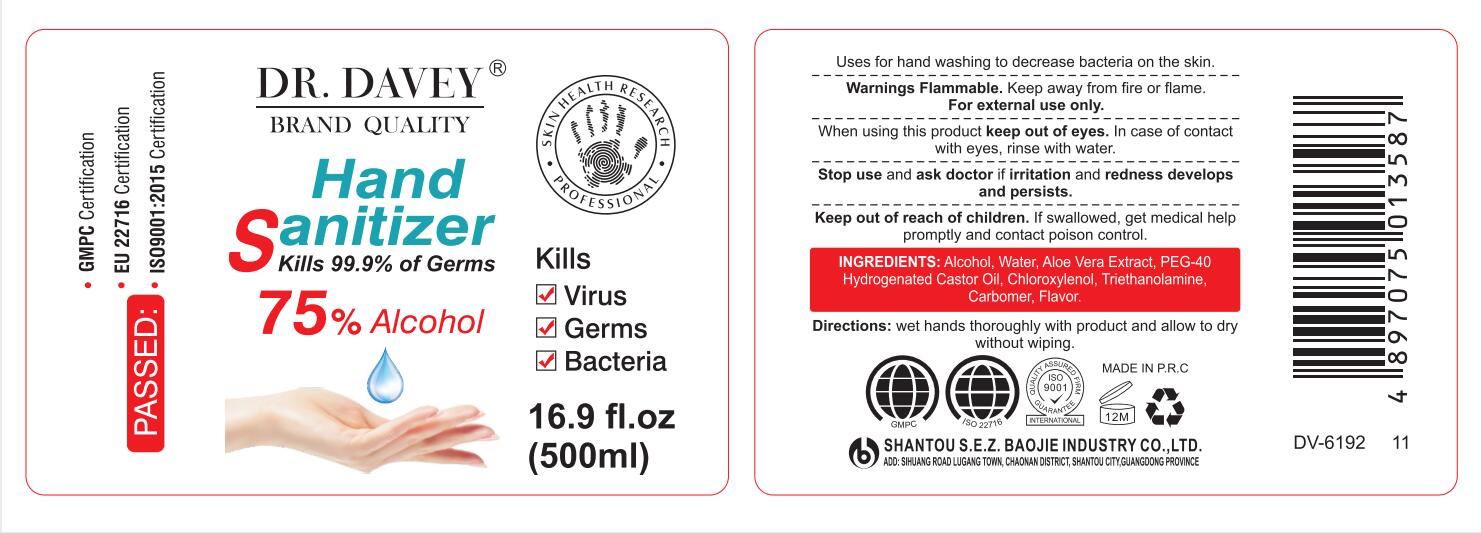 DRUG LABEL: Dr.Davey Hand Sanitizer
NDC: 74913-366 | Form: GEL
Manufacturer: SHANTOU S.E.Z BAOJIE INDUSTRY CO., LTD
Category: otc | Type: HUMAN OTC DRUG LABEL
Date: 20200821

ACTIVE INGREDIENTS: ALCOHOL 75 mL/100 mL
INACTIVE INGREDIENTS: HYDROGENATED CASTOR OIL 0.6 mL/100 mL; TROLAMINE 0.3 mL/100 mL; CHLOROXYLENOL 0.5 mL/100 mL; WATER 23.1 mL/100 mL; CARBOMER 940 0.5 mL/100 mL

Dr.Davey hand sanitizer DV-6192 36

Active Ingredient(s)

Alcohol 75% v/v. Purpose: Antiseptic

Purpose

Antiseptic, Hand Sanitizer

Use

Uses for hand washing to decrease bacteria on the skin.

Warnings

For external use only. Flammable. Keep away from heat or flame

Do not use

- in children less than 2 months of age
- on open skin wounds

When using this product keep out of eyes, ears, and mouth. In case of contact with eyes, rinse eyes thoroughly with water.

Stop use and ask a doctor if irritation or rash occurs. These may be signs of a serious condition.

Keep out of reach of children. If swallowed, get medical help or contact a Poison Control Center right away.

Directions

- Wet hands thoroughly with product and allow to dry without wiping

Inactive ingredients

Water,Pet-40 Hydrogenated Castor oil, Chloroxylenol, Carbomer, Triethanolamine,Flavor